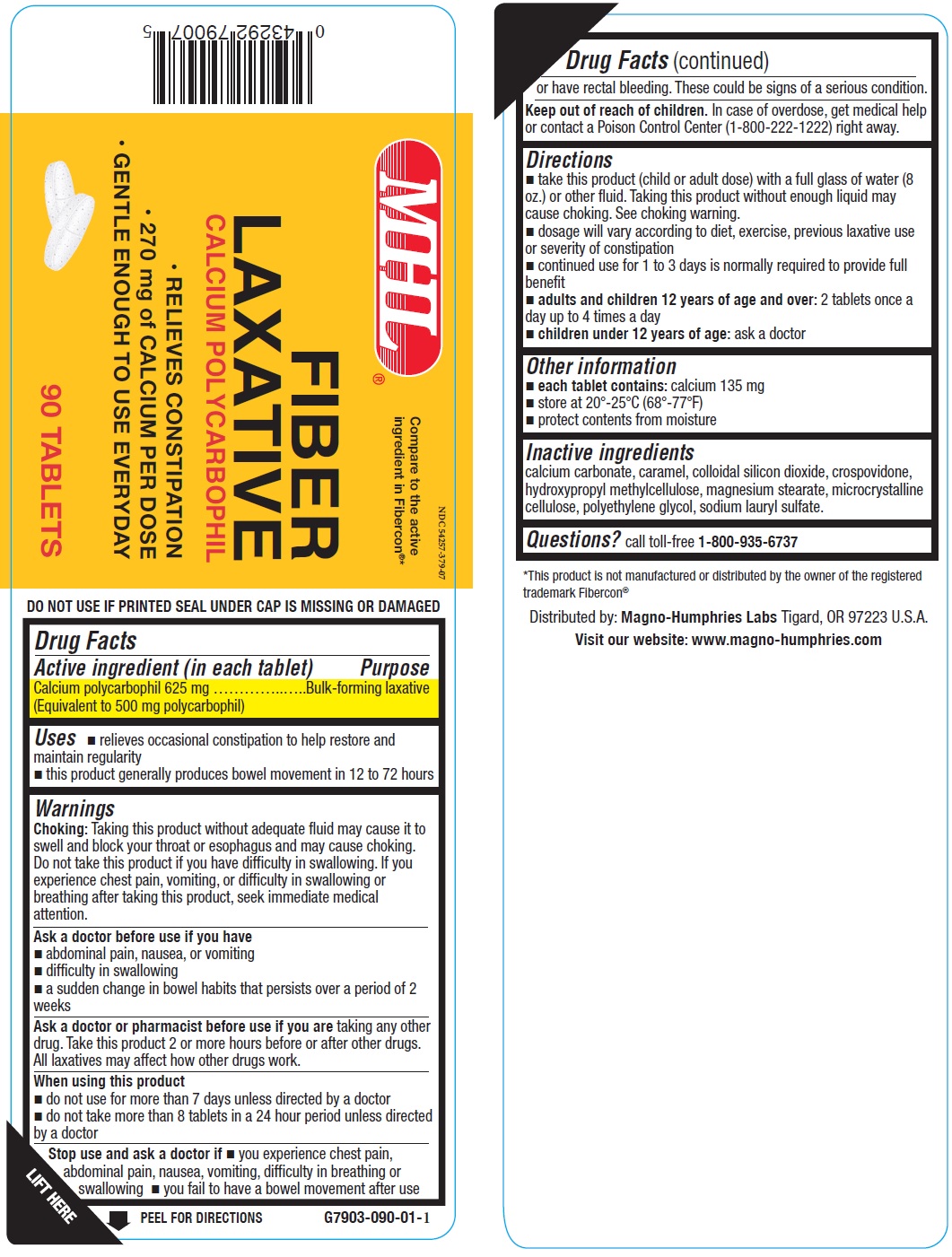 DRUG LABEL: Fiber Laxative
NDC: 54257-379 | Form: TABLET
Manufacturer: Magno-Humphries, Inc.
Category: otc | Type: HUMAN OTC DRUG LABEL
Date: 20231027

ACTIVE INGREDIENTS: CALCIUM POLYCARBOPHIL 625 mg/1 1
INACTIVE INGREDIENTS: CALCIUM CARBONATE; CARAMEL; SILICON DIOXIDE; CROSPOVIDONE; HYPROMELLOSE, UNSPECIFIED; MAGNESIUM STEARATE; MICROCRYSTALLINE CELLULOSE; POLYETHYLENE GLYCOL, UNSPECIFIED; SODIUM LAURYL SULFATE

Fiber Laxative

Active ingredient (in each tablet)

Calcium polycarbophil 625 mg (Equivalent to 500 mg polycarbophil)

Purpose

Bulk-forming laxative

Uses

- relieves occasional constipation to help restore and maintain regularity
- this product generally produces bowel movement in 12 to 72 hours

Warnings

Taking this product without adequate fluid may cause it to swell and block your throat or esophagus and may cause choking. Do not take this product if you have difficulty in swallowing. If you experience chest pain, vomiting, or difficulty in swallowing or breathing after taking this product, seek immediate medical attention. Choking:

Ask a doctor before use if you have

- abdominal pain, nausea, or vomiting
- difficulty in swallowing
- a sudden change in bowel habits that persists over a period of 2 weeks

Ask a doctor or pharmacist before use if you are

taking any other drug. Take this product 2 or more hours before or after other drugs. All laxatives may affect how other drugs work.

When using this product

- do not use for more than 7 days unless directed by a doctor
- do not take more than 8 tablets in a 24 hour period unless directed b y a doctor

Stop use and ask a doctor if

- you experience chest pain, abdominal pain, nausea, vomiting, difficulty in breathing or swallowing
- you fail to have a bowel movement after use or have rectal bleeding. These could be signs of a serious condition.

Keep out of reach of children.

In case of overdose, get medical help or contact a Poison Control Center (1-800-222-1222) right away.

Directions

- take this product (child or adult dose) with a full glass of water (8 oz.) or other fluid. Taking this product without enough liquid may cause choking. See choking warning.
- dosage will vary according to diet, exercise, previous laxative use or severity of constipation
- continued use for 1 to 3 days is normally required to provide full benefit
- 2 tablets once a day up to 4 times a day adults and children 12 years of age and over:
- ask a doctor children under 12 years of age:

Other information

- calcium 135 mg each tablet contains:
- store at 20°-25°C (68°-77°F)
- protect contents from moisture

Inactive ingredients

calcium carbonate, caramel, colloidal silicon dioxide, crospovidone, hydroxypropyl methylcellulose, magnesium stearate, microcrystalline cellulose, polyethylene glycol, sodium lauryl sulfate.

Questions?

call toll-free 1-800-935-6737